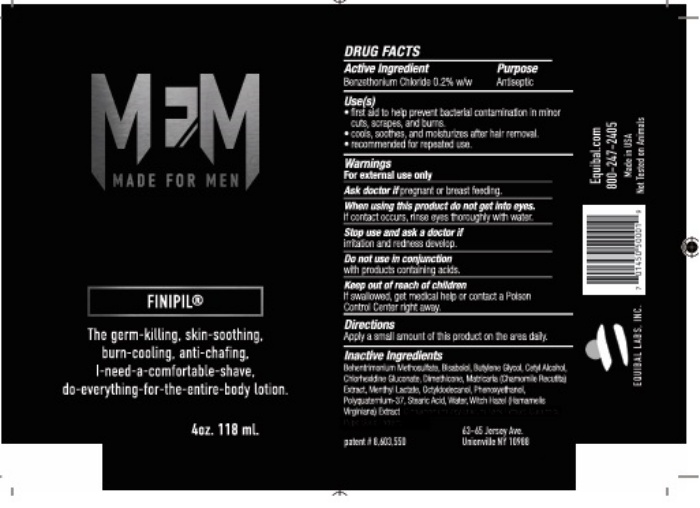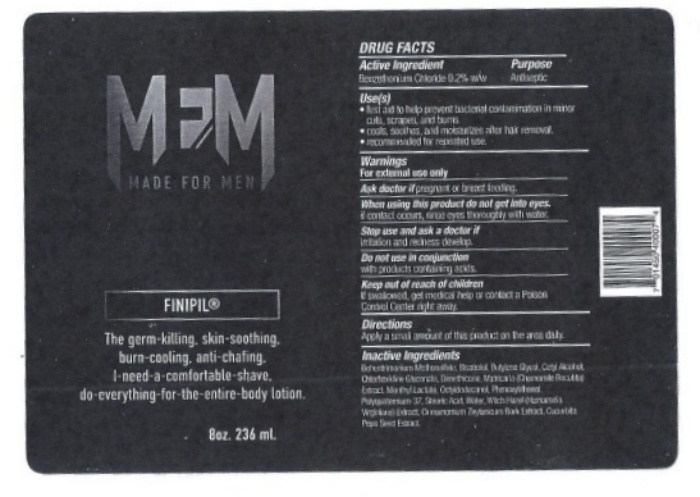 DRUG LABEL: Made for Men
NDC: 53228-232 | Form: LOTION
Manufacturer: Equibal, Inc.
Category: otc | Type: HUMAN OTC DRUG LABEL
Date: 20251217

ACTIVE INGREDIENTS: BENZETHONIUM CHLORIDE 0.2 mg/1 mg
INACTIVE INGREDIENTS: WATER

Made for Men

Active Ingredient

Benzethonium Chloride 0.2% w/w

Purpose

Antiseptic

Keep out of reach of children

if swallowed, get medical help or contact a Poison Control Center right away.

Uses

Uses(s)

- first aid to help prevent bacterial contamination in minor cuts, scrapes, and burns.
- cools, soothes, and moisturizes after hair removal.
- recommended for repeated use.

Warnings

For external use only

Ask Doctor

Ask a doctor ifpregnant or breast feeding.

Stop Use

Stop use and ask a doctor if

irritation and redness develop

Administration

Directions

Apply a small amount of this product on the area daily.

Inactive Ingredients

Behentrimonium Methosulfate, Bisabolol, Butylene Glycol, Cetyl Alcohol, Chlorhexidine Gluconate, Dimethicone, Matricaria (Chamomile Recutital) Extract, Menthyl Lactate, Octylodecanoil, Phenoxyethanol, Polyquaterniuim-37, Stearic Acid, Water, Witch Hazel (Hamamelis Virginiana) Extract, Cinnamomum Zeytuncum Bark Extract, Cucurbita Pepo Seed Extract

Package Label

MFM

MADE FOR MEN

FINIPIL®

The germ-killing, skin-soothing, burn-cooling, anti-chafing, I-need-a-comfortable-shave, do-everything-for-the-entire-body-lotion.

8 oz. 236 ml.

DRUG FACTS

Active Ingredient Purpose

Benzethonium Chloride 0.2% w/w Antiseptic

Uses(s)

- first aid to help prevent bacterial contamination in minor cuts, scrapes, and burns.
- cools, soothes, and moisturizes after hair removal.
- recommended for repeated use.

Warnings

For external use only

Ask a doctor ifpregnant or breast feeding.

When using this product do not get into eyes.

if contact occurs, rinse eyes thoroughly with water

Stop use and ask a doctor if

irritation and redness develop

Do not use in conjunction

with products containing acids.

Keep out of reach of children

if swallowed, get medical help or contact a Poison Control Center right away.

Directions

Apply a small amount of this product on the area daily.

Inactive Ingredients

Behentrimonium Methosulfate, Bisabolol, Butylene Glycol, Cetyl Alcohol, Chlorhexidine Gluconate, Dimethicone, Matricaria (Chamomile Recutital) Extract, Menthyl Lactate, Octylodecanoil, Phenoxyethanol, Polyquaterniuim-37, Stearic Acid, Water, Witch Hazel (Hamamelis Virginiana) Extract, Cinnamomum Zeytuncum Bark Extract, Cucurbita Pepo Seed Extract

Package Label

MFM

MADE FOR MEN

FINIPIL®

The germ-killing, skin-soothing, burn-cooling, anti-chafing, I-need-a-comfortable-shave, do-everything-for-the-entire-body-lotion.

8 oz. 236 ml.

DRUG FACTS

Active Ingredient Purpose

Benzethonium Chloride 0.2% w/w Antiseptic

Uses(s)

first aid to help prevent bacterial contamination in minor cuts, scrapes, and burns.
cools, soothes, and moisturizes after hair removal.
recommended for repeated use.

Warnings

For external use only

Ask a doctor if pregnant or breast feeding.

When using this product do not get into eyes.

if contact occurs, rinse eyes thoroughly with water

Stop use and ask a doctor if

irritation and redness develop

Do not use in conjunction

with products containing acids.

Keep out of reach of children

if swallowed, get medical help or contact a Poison Control Center right away.

Directions

Apply a small amount of this product on the area daily.

Inactive Ingredients

Behentrimonium Methosulfate, Bisabolol, Butylene Glycol, Cetyl Alcohol, Chlorhexidine Gluconate, Dimethicone, Matricaria (Chamomile Recutital) Extract, Menthyl Lactate, Octylodecanoil, Phenoxyethanol, Polyquaterniuim-37, Stearic Acid, Water, Witch Hazel (Hamamelis Virginiana) Extract, Cinnamomum Zeytuncum Bark Extract, Cucurbita Pepo Seed Extract